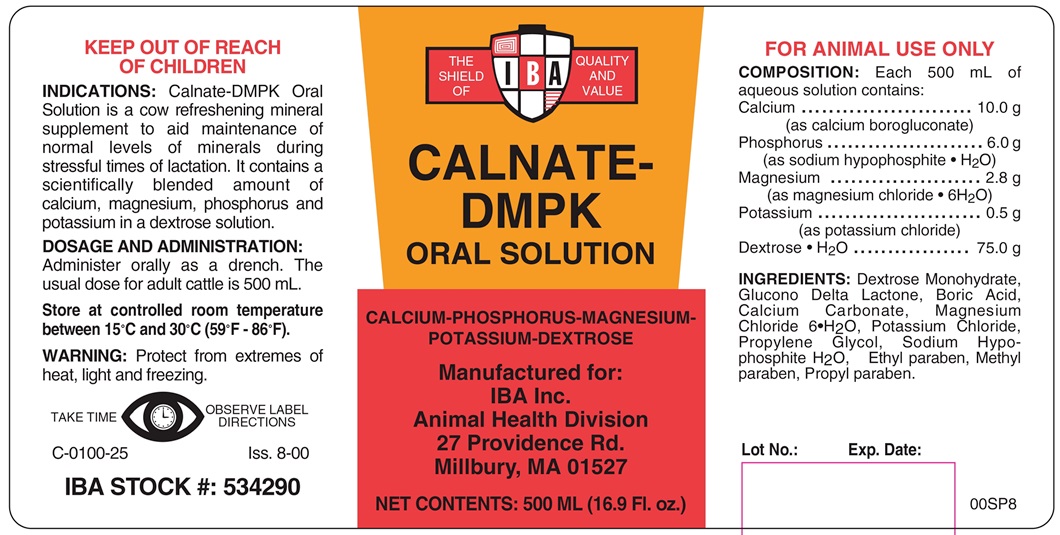 DRUG LABEL: CALNATE-DMPK
NDC: 29983-2712 | Form: SOLUTION
Manufacturer: IBA, Inc.
Category: animal | Type: OTC ANIMAL DRUG LABEL
Date: 20180430

ACTIVE INGREDIENTS: CALCIUM CARBONATE 9 g/500 mL; SODIUM HYPOPHOSPHITE MONOHYDRATE 5.4 g/500 mL; MAGNESIUM CHLORIDE 2.5 g/500 mL; POTASSIUM CHLORIDE 0.45 g/500 mL; DEXTROSE MONOHYDRATE 75 g/500 mL

CMPK Solution

INDICATIONS AND USAGE

ORAL SOLUTION

Calcium-Phosphorus-Magnesium-Potassium-Dextrose Oral Solution

KEEP OUT OF REACH OF CHILDREN

FOR ANIMAL USE ONLY

INDICATIONS

Calnate-DMPK Oral Solution is a cow refreshening mineral supplement to aid maintenance of normal levels of minerals during stressful times of lactation. It contains a scientifically blended amount of calcium, magnesium, phosphorus and potassium in a dextrose solution.

DOSAGE AND ADMINISTRATION

Administer orally as a drench. The usual dose for adult cattle is 500 mL.

STORAGE AND HANDLING

Store at controlled room temperature between 15° and 30°C (59°-86°F)

TAKE TIME OBSERVE LABEL DIRECTIONS

WARNINGS

Protect for extremes of heat, light and freezing.

COMPONENTS

COMPOSITION:

Each 500 mL of aqueous solution contains:

Calcium ............................... 10.0 g

(as calcium borogluconate)

Phosphorus .......................... 6.0 g

(as sodium hypophosphite·H2O)

Magnesium ........................... 2.8 g

(as magnesium chloride·6H2O)

Potassium ............................ 0.5 g

(as potassium chloride)

Dextrose·H2O ..................... 75.0 g

INGREDIENTS: Dextrose Monohydrate, Glucono Delta Lactone, Boric Acid, Calcium Carbonate, Magnesium Chloride 6·H2O, Potassium Chloride, Propylene Glycol, Sodium Hypophosphite H2O, Ethyl paraben, Methyl paraben, Propyl paraben.